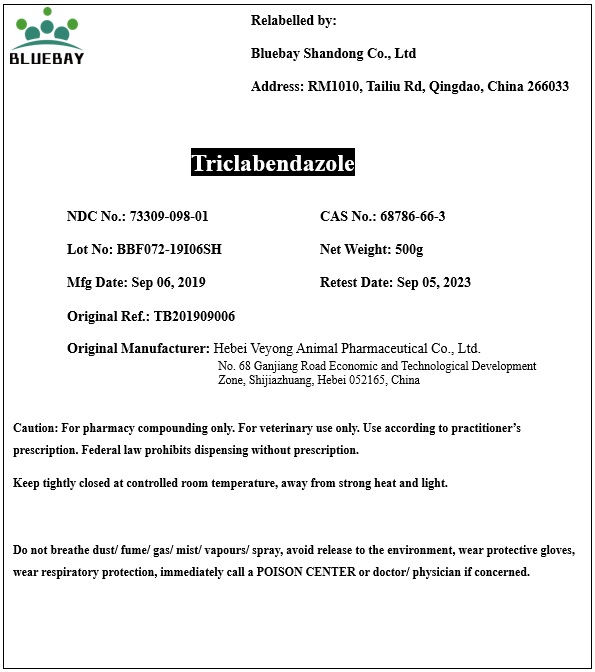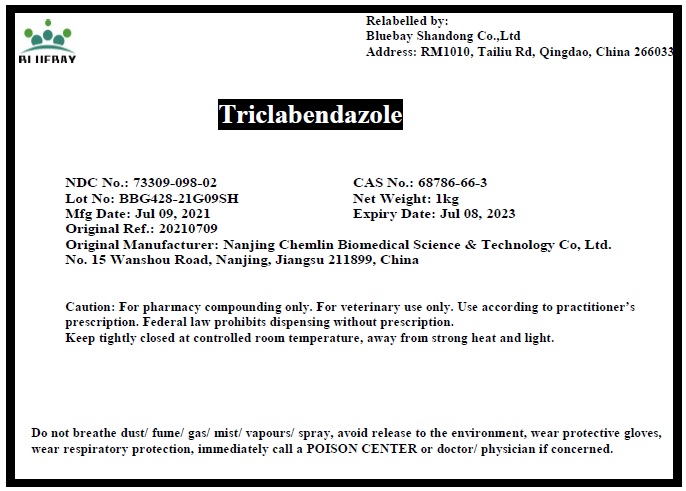 DRUG LABEL: Triclabendazole
NDC: 73309-098 | Form: POWDER
Manufacturer: BLUEBAY SHANDONG CO.,LTD
Category: other | Type: BULK INGREDIENT
Date: 20210816

ACTIVE INGREDIENTS: TRICLABENDAZOLE 1 g/1 g

Triclabendazole